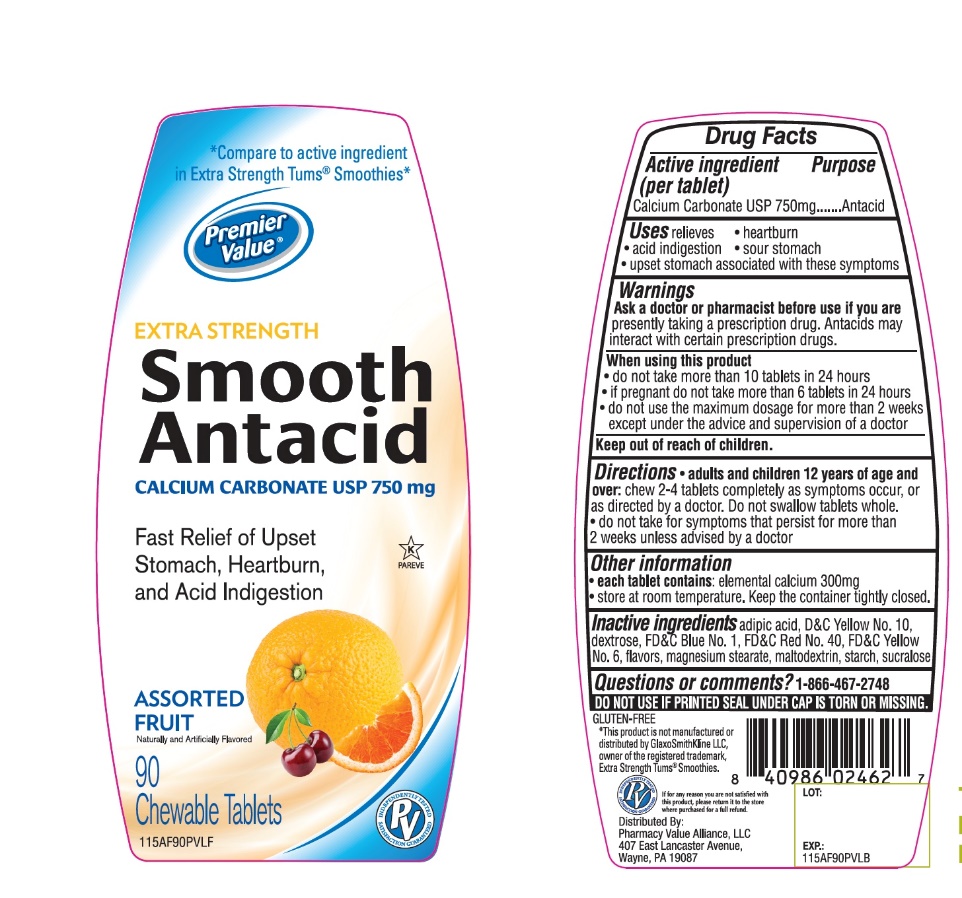 DRUG LABEL: Premier Value Smooth Antacid Extra Strength
NDC: 68016-675 | Form: TABLET, CHEWABLE
Manufacturer: Chain Drug Consortium
Category: otc | Type: HUMAN OTC DRUG LABEL
Date: 20241028

ACTIVE INGREDIENTS: CALCIUM CARBONATE 500 mg/1 1
INACTIVE INGREDIENTS: ADIPIC ACID; DEXTROSE, UNSPECIFIED FORM; FD&C BLUE NO. 1; MAGNESIUM STEARATE; MALTODEXTRIN; D&C RED NO. 27; STARCH, CORN; SUCRALOSE; FD&C YELLOW NO. 6; D&C YELLOW NO. 10

Premier Value Extra Strength Smooth Antacid

Active ingredient

Calcium Carbonate USP 750mg

Purpose

Antacid

Uses

relieves:

• heartburn

• sour stomach

• acid indigestion

• upset stomach associated with these symptoms

Warnings

Ask a doctor or pharmacist before use if you are taking a prescription drug. Antacids may interact with certain prescription drugs.

When using this product

• do not take more than 10 tablets in 24 hours

• if pregnant do not take more than 6 tablets in 24 hours

• do not use the maximum dosage for more than 2 weeks except under the advice and supervision of a doctor

Directions

• adults and children 12 years of age and over: chew 2-4 tablets completely as symptoms occur, or as directed by a doctor. Do not swallow tablets whole.

• do not take for symptoms that persist for more than 2 weeks unless advised by a doctor.

Other Information

• each tablet contains: elemental calcium 300mg

• Store at room temperature. Keep the container tightly closed

Inactive ingredients

adipic acid, blue 1 lake, dextrose, flavors, magnesium stearate, maltodextrin, red 27 lake, starch, sucralose, yellow 6 lake, yellow 10 lake.

Safety sealed: Do not use if printed seal under cap is torn or missing

Package/Label Principal Display Panel

Compare to the Active Ingredient in Tums Smoothies™ E-X*

Premier Value

Extra Strength

Smooth Antacid Tablets

Assorted Fruit Flavor

Calcium Rich

For Fast Relief of Heartburn, Acid Indigestion & Upset Stomach

90 Smooth Dissolve Chewable Tablets

Distributed by

Chain Drug Consortium, LLC.

3301 N.W. Boca Raton Blvd.,

Suite 101, Boca Raton FL 33431

This product is not manufactured or distributed by GlaxoSmithKline, the distributor of Tums®